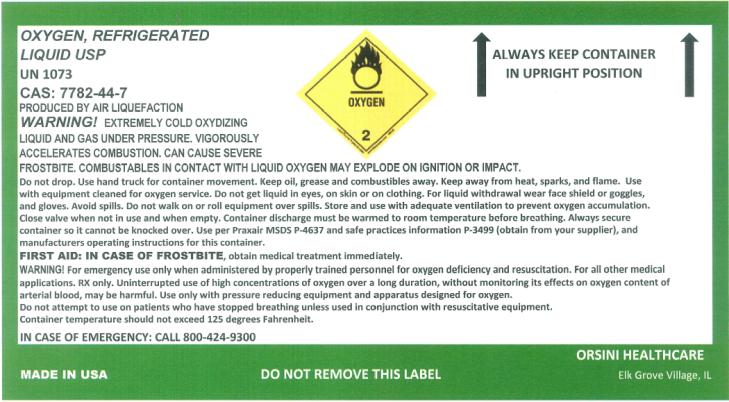 DRUG LABEL: Oxygen
NDC: 49936-1303 | Form: GAS
Manufacturer: Orsini Home Medical Equipment Inc.
Category: prescription | Type: HUMAN PRESCRIPTION DRUG LABEL
Date: 20091114

ACTIVE INGREDIENTS: OXYGEN 1 L/1 L

Oxygen

OXYGEN, REFRIGERATED

LIQUID USP

UN 1073

CAS: 7782-44-7

PRODUCED BY AIR LIQUEFACTION

WARNING!

EXTREMELY COLD OXYDIZING LIQUID AND GAS UNDER PRESSURE. VIGOROUSLY ACCELERATES COMBUSTION. CAN CAUSE SEVERE FROSTBITE. COMBUSTABLES IN CONTACT WITH LIQUID OXYGEN MAY EXPLODE ON IGNITION OR IMPACT.

Do not drop. Use hand truck for container movement. Keep oil, grease and combustibles away. Keep away from heat, sparks, and flame. Use with equipment cleaned for oxygen service. Do not get liquid in eyes, on skin or on clothing. For liquid withdrawal wear face shield or goggles, and gloves. Avoid spills. Don not walk on or roll equipment over spills. Store and use with adequate ventilation to prevent oxygen accumulation. Close valve when not in use and when empty. Container discharge must be warmed to room temperature before breathing. Always secure container so it cannot be knocked over. Use per Praxair MSDS P-4637 and safe practices information P-3499 (obtain from your supplier) and manufactures operating instructions for this container.

FIRST AID: IN CASE OF FROSTBITE, obtain medical treatment immediately.

WARNING! For emergency use only when administered by properly trained personnel for Oxygen deficiency and resuscitation. For all other medical applications, RX only. Uninterrupted use of high concentrations of oxygen over a long duration, without monitoring its effect on oxygen content of arterial blood, may be harmful. Use only with pressure reducing equipment and apparatus designed for oxygen. Do not attempt to use on patients who have stopped breathing unless used in conjunction with resuscitative equipment. Container temperature should not exceed 125 degrees Fahrenheit.

IN CASE OF EMERGENCY: CALL 800-424-9300

ORSINI HEALTHCARE

MADE IN USA DO NOT REMOVE THIS LABEL Elk Grove Village, IL

PRINCIPAL DISPLAY PANEL

OXYGEN, REFRIGERATED

LIQUID USP

UN 1073

CAS: 7782-44-7